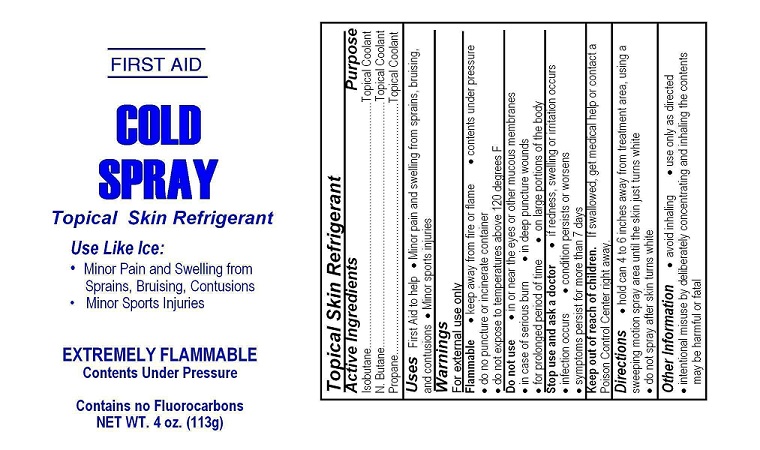 DRUG LABEL: Your Label Here Cold Spray
NDC: 52982-103
Manufacturer: Dixon Investments, Inc.
Category: other | Type: OTC MEDICAL DEVICE LABEL
Date: 20130409

YOUR LABEL HERE COLD SPRAY

Active Ingredients

Isobutane
N-Butane
Propane

Purpose

Topical Coolant
Topical Coolant
Topical Coolant

Uses

First Aid to help
Minor pain and swelling from sprains, bruising, and contusions
Minor sports injuries

Warnings

For external use only

Flammable

keep away from fire or flame
contents under pressure
do not puncture or incinerate container
do not expose to temperatures above 120°F

Do not use

in or near eyes or other mucous membranes
in case of serious burn
in deep puncture wounds
for prolonged period of time
on large portions of the body

Stop use and ask a doctor

If redness, swelling or irritation occurs
infection occurs
condition persists or worsens
symptoms persist for more than 7 days

Keep out of reach of children

If swallowed, get medical help or contact a Poison Control Center right away

Directions

hold can 4 to 6 inches away from treatment area, using a sweeping motion spray area until the skin just turns white
do not spray after skin turns white

Other Information

avoid inhaling
use only as directed
intentional misuse by deliberately concentrating and inhaling the contents may be harmful or fatal